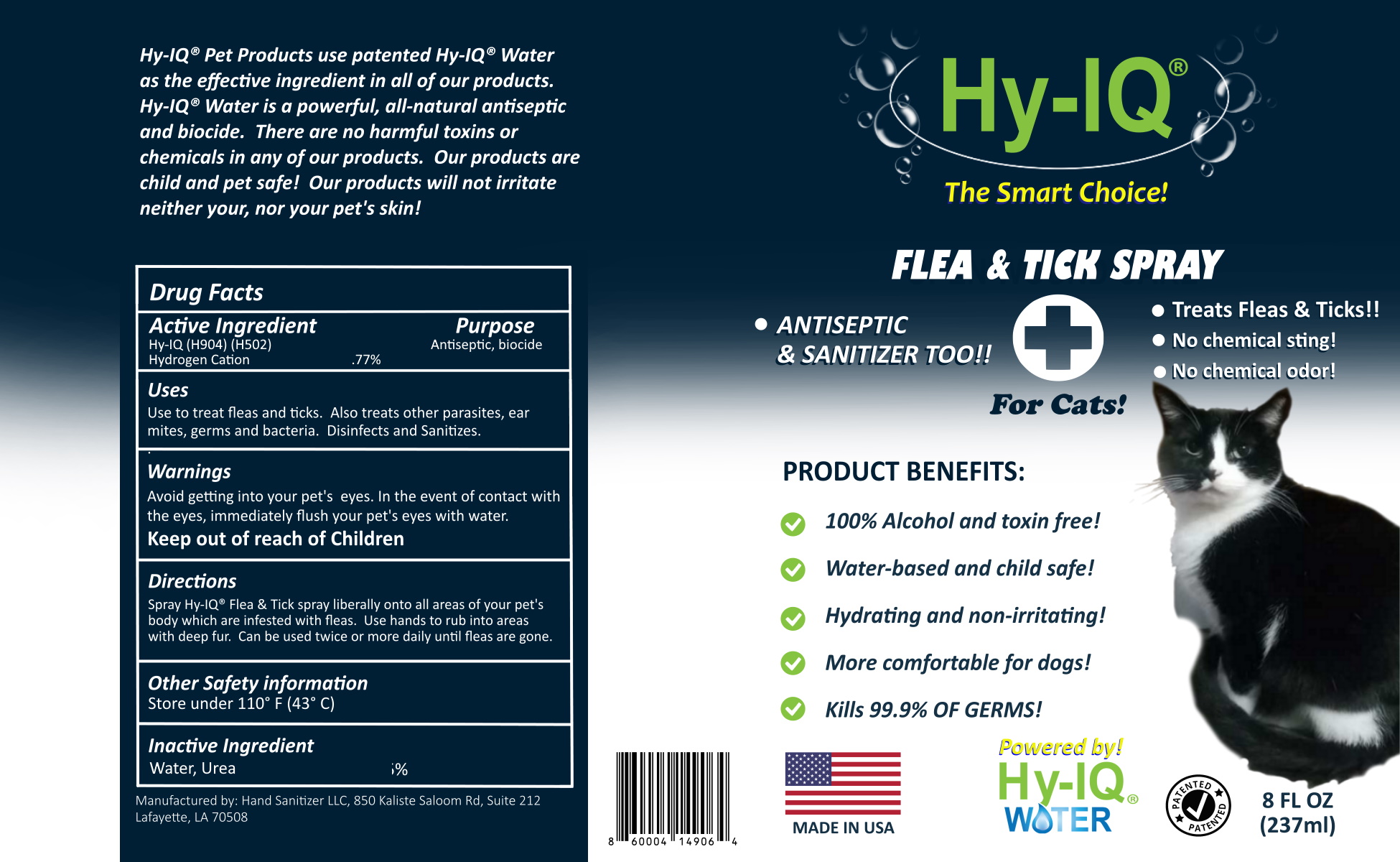 DRUG LABEL: HY IQ FLEA AND TICK FOR CATS
NDC: 76701-216 | Form: SPRAY
Manufacturer: HAND SANITIZER LLC
Category: animal | Type: OTC ANIMAL DRUG LABEL
Date: 20210625

ACTIVE INGREDIENTS: HYDROGEN CATION 10 mg/1 mL
INACTIVE INGREDIENTS: WATER 940 mg/1 mL; UREA 50 mg/1 mL

HY IQ FLEA AND TICK FOR CATS

ACTIVE INGREDIENTS

HY-IQ WATER ([H9O4] | [H502])

HYDROGEN CATION .77%

PURPOSE

ANTISEPTIC

USES

USE TO TREAT FLEAS AND TICKS, ALSO TREATS FLEAS & TICKS AS WELL AS OTHER PARASITES, EAR MITES, GERMS AND BACTERIA. DISINFECTS AND SANITIZES

WARNINGS

AVOID GETTING INTO YOUR PET'S EYES. IN THE EVENT OF CONTACT WITH THE EYES, IMMEDIATELY FLUSH YOUR PET'S EYES WITH WATER.
KEEP OUT OF REACH OF CHILDREN

DIRECTIONS

SPRAY HY-IQ® FLEA & TICK SPRAY LIBERALLY ONTO ALL AREAS OF YOUR PET'S BODY WHICH ARE INFESTED WITH FLEAS. USE HANDS TO RUB INTO AREAS WITH DEEP FUR. CAN BE USED TWICE OR MORE DAILY UNTIL FLEAS ARE GONE.

OTHER SAFETY INFORMATION

STORE UNDER 110° F (43°C)

INACTIVE INGREDIENTS

WATER, UREA